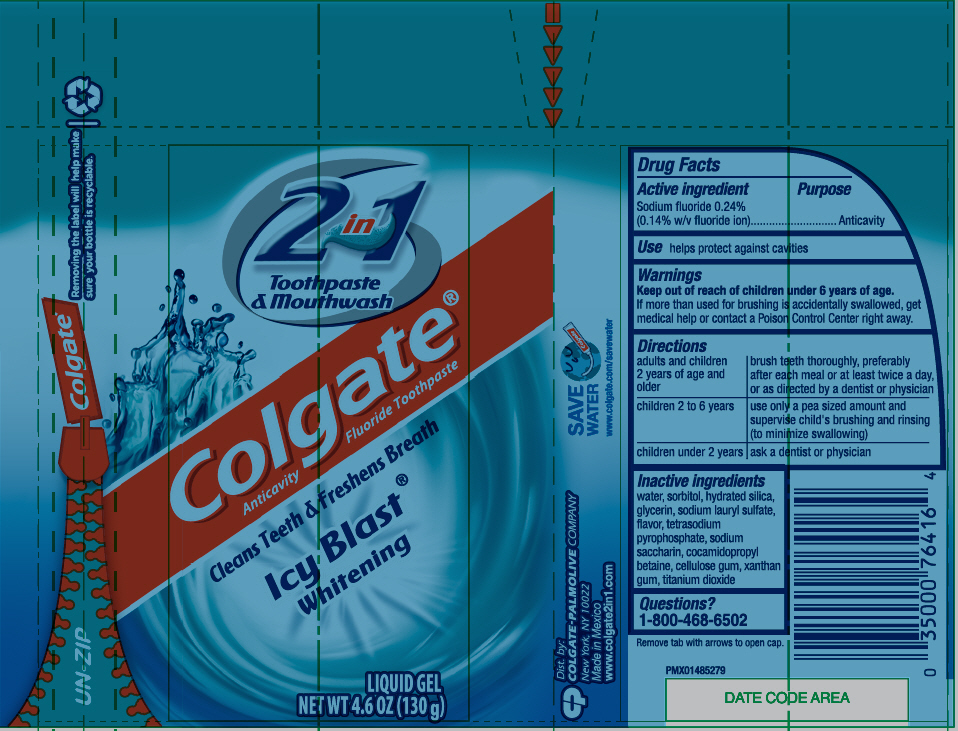 DRUG LABEL: COLGATE 2IN1
NDC: 35000-927 | Form: GEL, DENTIFRICE
Manufacturer: Colgate-Palmolive Company
Category: otc | Type: HUMAN OTC DRUG LABEL
Date: 20191205

ACTIVE INGREDIENTS: SODIUM FLUORIDE 1.1 mg/1 g
INACTIVE INGREDIENTS: SORBITOL 331.2 mg/1 g; WATER 394.54 mg/1 g; GLYCERIN; HYDRATED SILICA; SODIUM LAURYL SULFATE; COCAMIDOPROPYL BETAINE; SODIUM PYROPHOSPHATE; SACCHARIN SODIUM; MICA; TITANIUM DIOXIDE; CARBOXYMETHYLCELLULOSE SODIUM, UNSPECIFIED; XANTHAN GUM

COLGATE® 2IN1 TOOTHPASTE AND MOUTHWASH ICY BLAST® LIQUID GEL

Drug Facts

Active ingredient

Sodium fluoride 0.24% (0.14% w/v fluoride ion)

Purpose

Anticavity

Use

aids in the prevention of cavities

Warnings

KEEP OUT OF REACH OF CHILDREN

Keep out of the reach of children under 6 years of age.

If more than used for brushing is accidentally swallowed, get medical help or contact a Poison Control Center right away.

Directions

adults and children 2 years of age and older | brush teeth thoroughly, preferably after each meal or at least twice a day, or as directed by a dentist or physician
children 2 to 6 years | use only a pea sized amount and supervise child's brushing and rinsing (to minimize swallowing)
children under 2 years | ask a dentist or physician

Inactive ingredients

water, sorbitol, hydrated silica, glycerin, sodium lauryl sulfate, flavor, tetrasodium pyrophosphate, sodium saccharin, cocamidopropyl betaine, cellulose gum, xanthan gum, mica, titanium dioxide

Questions?

Call toll-free 1-800-468-6502

Dist. by:
COLGATE-PALMOLIVE COMPANY
New York, NY 10022

PRINCIPAL DISPLAY PANEL - 130 g Bottle Label

2 in 1
Toothpaste
& Mouthwash

Colgate®
Anticavity Fluoride Toothpaste

Cleans Teeth & Freshens Breath

Icy Blast ®
Whitening

LIQUID GEL
NET WT 4.6 OZ (130 g)